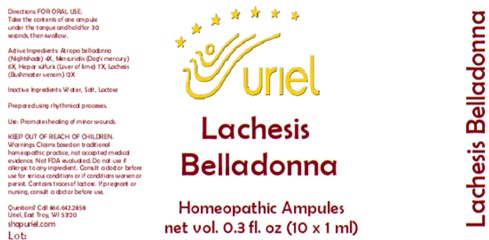 DRUG LABEL: Lachesis Belladonna
NDC: 48951-6012 | Form: LIQUID
Manufacturer: Uriel Pharmacy Inc.
Category: homeopathic | Type: HUMAN OTC DRUG LABEL
Date: 20250107

ACTIVE INGREDIENTS: ATROPA BELLADONNA 4 [hp_X]/1 mL; MERCURIALIS PERENNIS 6 [hp_X]/1 mL; CALCIUM SULFIDE 7 [hp_X]/1 mL; LACHESIS MUTA VENOM 12 [hp_X]/1 mL
INACTIVE INGREDIENTS: SODIUM CHLORIDE; WATER

Lachesis Belladonna

INDICATIONS AND USAGE

Directions: FOR ORAL USE.

DOSAGE AND ADMINISTRATION

Take the contents of one ampule under the tongue and hold for 30 seconds, then swallow.

ACTIVE INGREDIENT

Active Ingredients: Atropa belladonna (Nightshade) 4X, Mercurialis (Dog’s mercury) 6X, Hepar sulfuris (Liver of lime) 7X, Lachesis (Bushmaster venom) 12X

Inactive Ingredients: Water, Salt

Prepared using rhythmical processes.

PURPOSE

Use: Promotes healing of minor wounds.

KEEP OUT OF REACH OF CHILDREN.

WARNINGS

Warnings: Claims based on traditional homeopathic practice, not accepted medical evidence. Not FDA evaluated. Do not use if allergic to any ingredient. Consult a doctor before use for serious conditions or if conditions worsen or persist. Contains traces of lactose. If pregnant or nursing, consult a doctor before use.

QUESTIONS

Questions? Call 866.642.2858 Uriel, East Troy, WI 53120 shopuriel.com